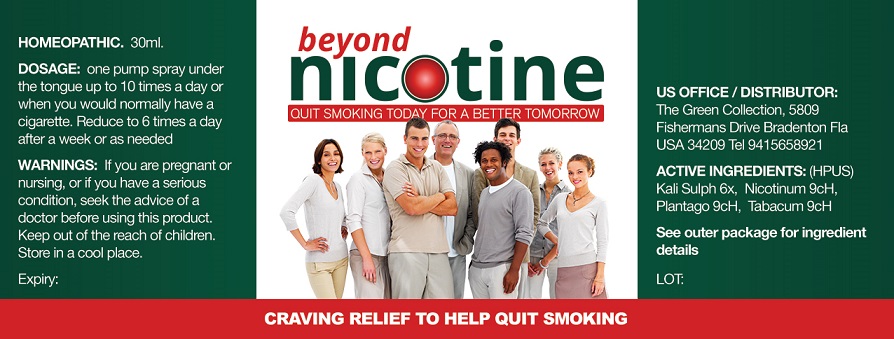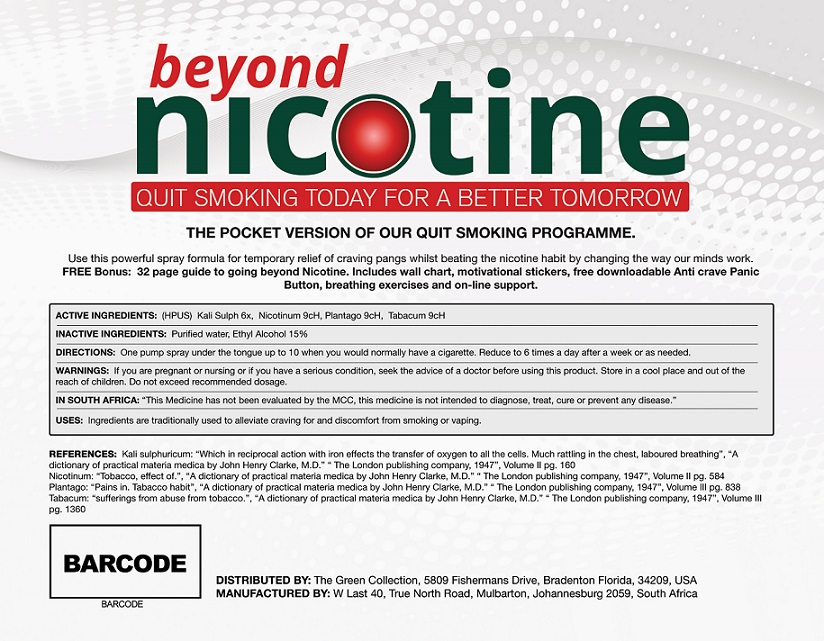 DRUG LABEL: Beyond Nicotine
NDC: 58214-789 | Form: SPRAY
Manufacturer: JMSP USA LLC
Category: homeopathic | Type: HUMAN OTC DRUG LABEL
Date: 20170612

ACTIVE INGREDIENTS: POTASSIUM SULFATE 6 [hp_X]/30 mL; NICOTINE 9 1/30 mL; PLANTAGO MAJOR 9 1/30 mL; TOBACCO LEAF 9 1/30 mL
INACTIVE INGREDIENTS: ALCOHOL; WATER

Beyond Nicotine

Active Ingrdietns

Kali Sulph 6x

Nicotinum 9cH

Plantago 9cH

Tabacum 9cH

Purpose of ingredients:

Traditionally used to alleviate craving for and discomfort from smoking or vaping.

Keep out of reach of children

Warnings:

- Not intended for pregnant or lactating women
- Not to be taken by those with existing medical conditions, please consult your physician prior to use.

Indications and Usage:

A pump spray under the tongue up to 10 when you would normally have a cigarette. Reduce to 6 times a day after a week or as needed

Inactive Ingredients:

Purified Water and Ethyl Alcohol

Directions

One pump spray under the tongue up to 10 times a day or when you would normally have a cigarette. Reduce to 6 times a day after a week or as needed